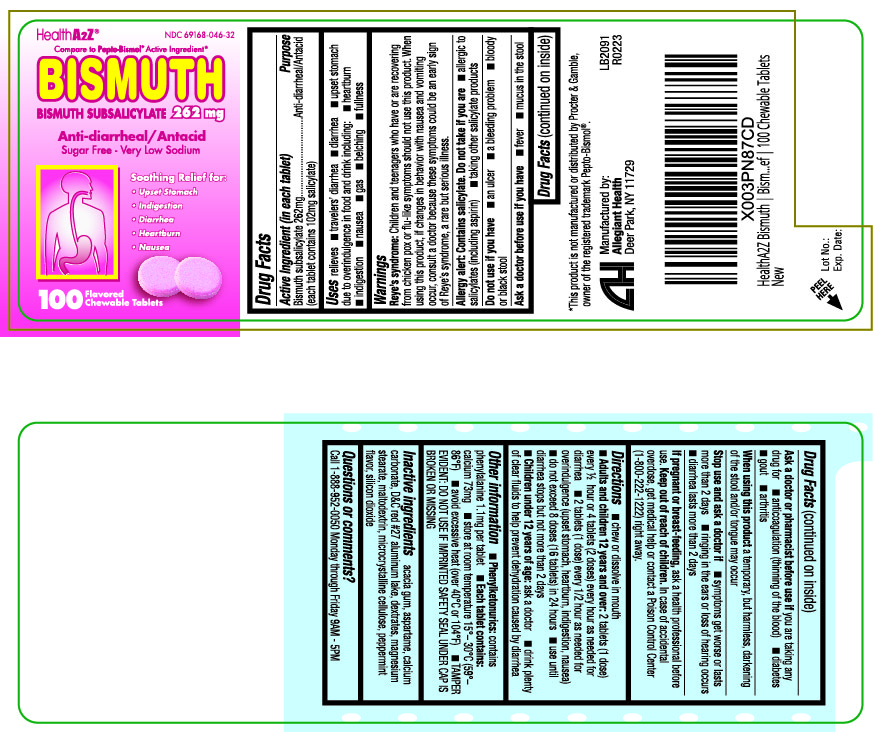 DRUG LABEL: Bismuth
NDC: 69168-046 | Form: TABLET
Manufacturer: Allegiant Health
Category: otc | Type: HUMAN OTC DRUG LABEL
Date: 20181107

ACTIVE INGREDIENTS: BISMUTH SUBSALICYLATE 262 mg/1 1
INACTIVE INGREDIENTS: ASPARTAME; CALCIUM CARBONATE; D&C RED NO. 27; DEXTRATES; MAGNESIUM STEARATE; CELLULOSE, MICROCRYSTALLINE; SILICON DIOXIDE; ACACIA; MALTODEXTRIN; PEPPERMINT

Drug Facts

Active ingredient

Bismuth subsalicylate 262 mg (each tablet contains 102 mg salicylate)

Purpose

Antidiarrheal/Antacid

Uses

- relieves
- travelers’ diarrhea
- diarrhea
- upset stomach due to overindulgence in food and drink including:
- heartburn
- indigestion
- nausea
- gas
- belching
- fullness

Warnings

Reye’s syndrome

Children and teenagers who have or are recovering from chicken pox or flu-like symptoms should not use this product. When using this product, if changes in behavior with nausea and vomiting occur, consult a doctor because these symptoms could be an early sign of Reye’s syndrome, a rare but serious illness.

Allergy alert

Contains salicylate. Do not take if you are allergic to salicylates (including aspirin) taking other salicylate products

Do not use if you have

- an ulcer
- a bleeding problem
- bloody or black stool

Ask a doctor before use if you have

- fever
- mucus in the stool

Ask a doctor or pharmacist before use if you

are taking any drug for

- anticoagulation (thinning the blood)
- diabetes
- gout
- arthritis

Stop use and ask a doctor if

- symptoms get worse or last more than 2 days
- ringing in the ears or loss of hearing occurs n diarrhea lasts more than 2 days

When using this product

a temporary, but harmless, darkening of the stool and/or tongue may occur

If pregnant or breast-feeding

ask a health professional before use.

Keep Out of Reach of Children

In case of accidental overdose, contact a doctor or Poison Control Center (1-800-222-1222) right away.

Directions

- chew or dissolve in mouth

Adults and children over 12 years : 2 tablets (1 dose) every ½ hour or 4 tablets (2 doses) every hour as needed for diarrhea

- 2 tablets (1 dose) every 1/2 hour as needed for overindulgence (upset stomach, heartburn, indigestion, nausea)
- do not exceed 8 doses (16 tablets) in 24 hours
- use until diarrhea stops but no more than 2 days

Children under 12 years of age: ask a doctor

- drink plenty of clear fluids to prevent dehydration caused by diarrhea

Inactive Ingredients

acacia gum, aspartame, calcium carbonate, D&C red #27 aluminum lake, dextrates, magnesium stearate, maltodextrin, microcrystalline cellulose, peppermint flavor, silicon dioxide

Package/Label Principal Display Panel

Bismuth